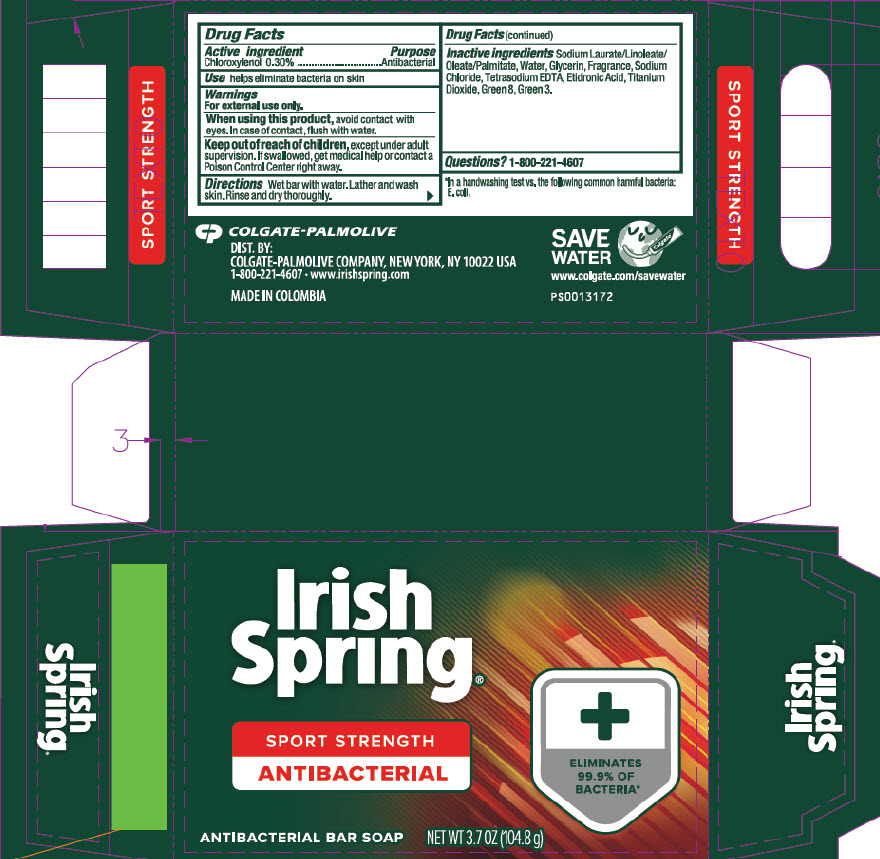 DRUG LABEL: Irish Spring Antibacterial Bar
NDC: 35000-068 | Form: SOAP
Manufacturer: Colgate-Palmolive Company
Category: otc | Type: HUMAN OTC DRUG LABEL
Date: 20201028

ACTIVE INGREDIENTS: CHLOROXYLENOL 3 mg/1 g
INACTIVE INGREDIENTS: SODIUM LAURATE; SODIUM LINOLEATE; SODIUM OLEATE; SODIUM PALMITATE; WATER; GLYCERIN; SODIUM CHLORIDE; EDETATE SODIUM; ETIDRONIC ACID; TITANIUM DIOXIDE; D&C GREEN NO. 8; FD&C GREEN NO. 3

Irish Spring® Antibacterial Bar

Drug Facts

Active ingredient

Chloroxylenol 0.30%

Purpose

Antibacterial

Use

helps eliminate bacteria on skin

Warnings

For external use only.

When using this product, avoid contact with eyes. In case of contract, flush with water.

Keep out of reach of children, except under adult supervision. If swallowed, get medical help or contact a Poison Control Center right away.

Directions

Wet bar with water. Lather and wash skin. Rinse and dry thoroughly.

Inactive ingredients

Sodium Laurate/Linoleate/Oleate/Palmitate, Water, Glycerin, Fragrance, Sodium Chloride, Tetrasodium EDTA, Etidronic Acid, Titanium Dioxide, Green 8, Green 3.

Questions?

1-800-221-4607

DIST. BY:
COLGATE-PALMOLIVE COMPANY, NEW YORK, NY 10022 USA

PRINCIPAL DISPLAY PANEL - 104.8 g Bar Carton

Irish
Spring®

SPORT STRENGTH
ANTIBACTERIAL

ELIMINATES
99.9% OF
BACTERIA*

ANTIBACTERIAL BAR SOAP

NET WT 3.7 OZ (104.8 g)